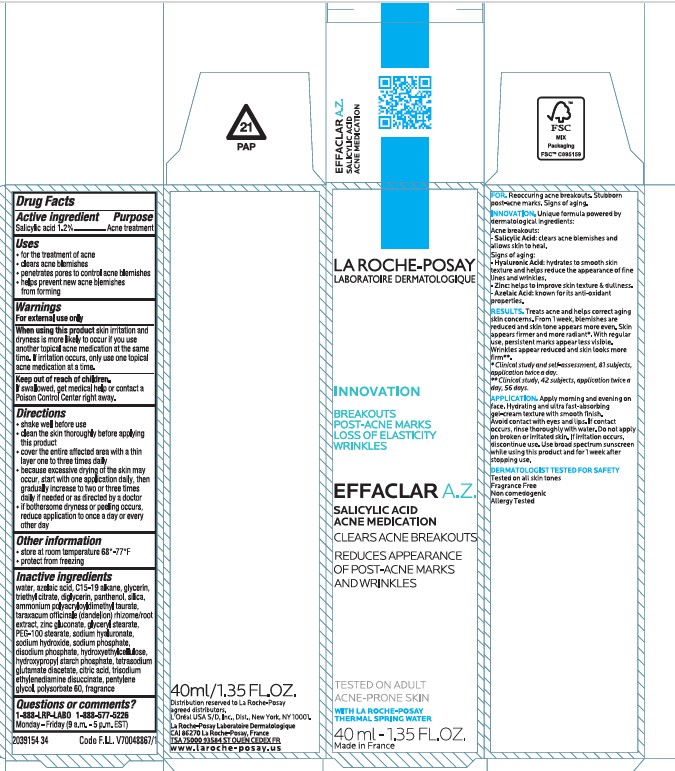 DRUG LABEL: La Roche Posay Laboratoire Dermatologique Effaclar AZ Acne Treatment
NDC: 49967-735 | Form: CREAM
Manufacturer: L'Oreal USA Products Inc
Category: otc | Type: HUMAN OTC DRUG LABEL
Date: 20250612

ACTIVE INGREDIENTS: SALICYLIC ACID 12 mg/1 mL
INACTIVE INGREDIENTS: WATER; AZELAIC ACID; C15-19 ALKANE; GLYCERIN; TRIETHYL CITRATE; DIGLYCERIN; PANTHENOL; SILICA; AMMONIUM POLYACRYLOYLDIMETHYL TAURATE; TARAXACUM OFFICINALE ROOT; ZINC GLUCONATE; GLYCERYL STEARATE; PEG-100 STEARATE; SODIUM HYALURONATE; SODIUM HYDROXIDE; SODIUM PHOSPHATE; DISODIUM PHOSPHATE; HYDROXYETHYLCELLULOSE; TETRASODIUM GLUTAMATE DIACETATE; CITRIC ACID; TRISODIUM ETHYLENEDIAMINE DISUCCINATE; PENTYLENE GLYCOL; POLYSORBATE 60

Drug Facts

Active ingredient

Salicylic acid 1.2%

Purpose

Acne treatment

Uses

- for the treatment of acne
- clears acne blemishes
- penetrates pores to control acne blemishes
- helps prevent new acne blemishes from forming

Warnings

For external use only

When using this product

skin irritation and dryness is more likely to occur if you use another topical acne medication at the same time. If irritation occurs, only use one topical acne medication at a time.

Keep out of reach of children.

If swallowed, get medical help or contact a Poison Control Center right away.

Directions

- shake well before use
- clean the skin thoroughly before applying this product
- cover the entire affected area with a thin layer one to three times daily
- because excessive drying of the skin may occur, start with one application daily, then gradually increase to two or three times daily if needed or as directed by a doctor
- if bothersome dryness or peeling occurs, reduce application to once a day or every other day
- if going outside, apply sunscreen after using this product. If irritation or sensitivity develops, stop use of both products and ask a doctor.

Other information

- store at room temperature 68⁰ – 77⁰F
- protect from freezing

Inactive ingredients

water, azelaic acid, C15-19 alkane, glycerin, triethyl citrate, diglycerin, panthenol, silica, ammonium polyacryloyldimethyl taurate, taraxacum officinale (dandelion) rhizome/root extract, zinc gluconate, glyceryl stearate, PEG-100 stearate, sodium hyaluronate, sodium hydroxide, sodium phosphate, disodium phosphate, hydroxyethylcellulose, hydroxypropyl starch phosphate, tetrasodium glutamate diacetate, citric acid, trisodium ethylenediamine disuccinate, pentylene glycol, polysorbate 60, fragrance

Questions or comments?

1-888-LRP LABO

1-888-577-5226

Monday - Friday (9 a.m. - 5 p.m. EST)